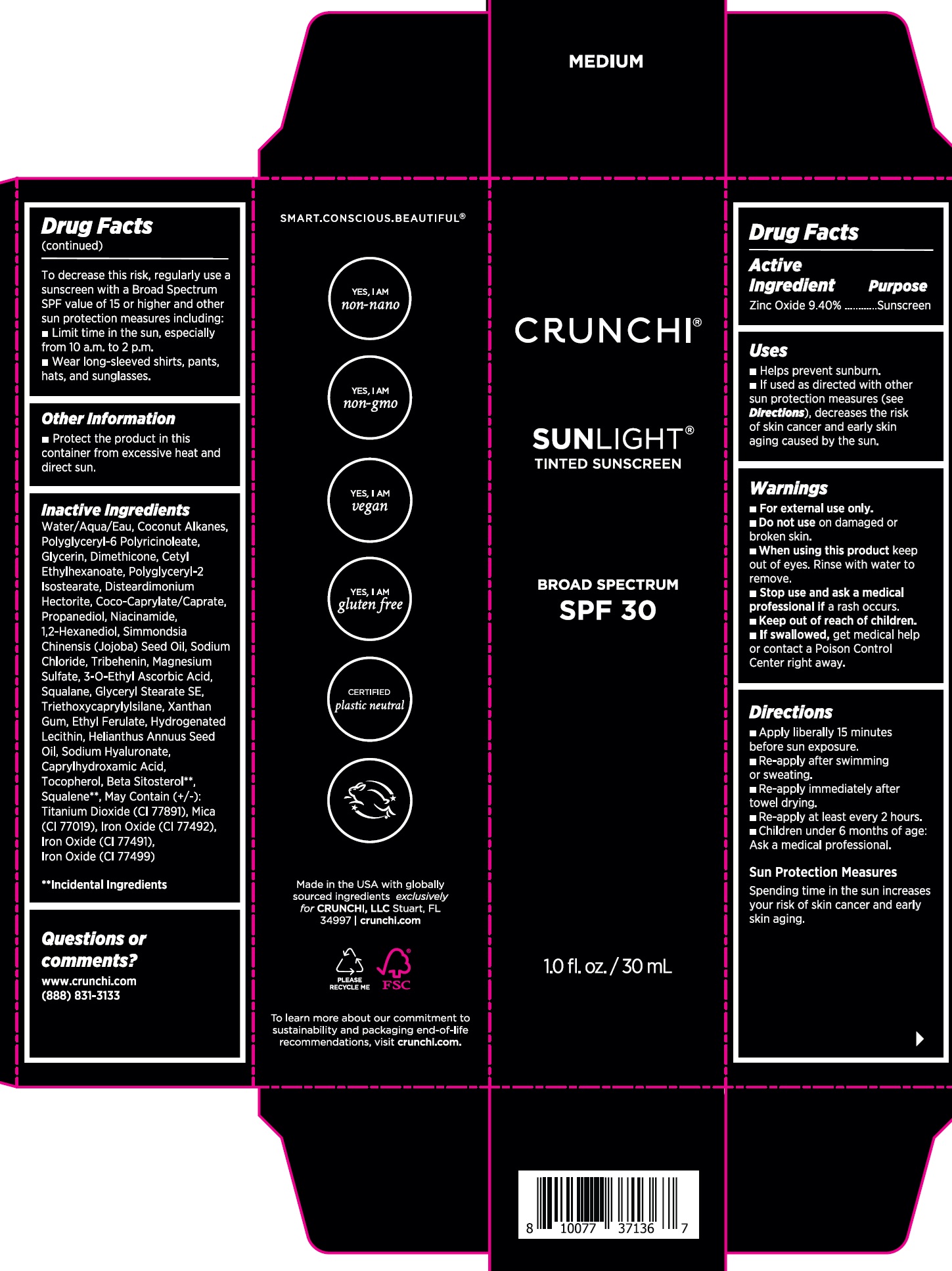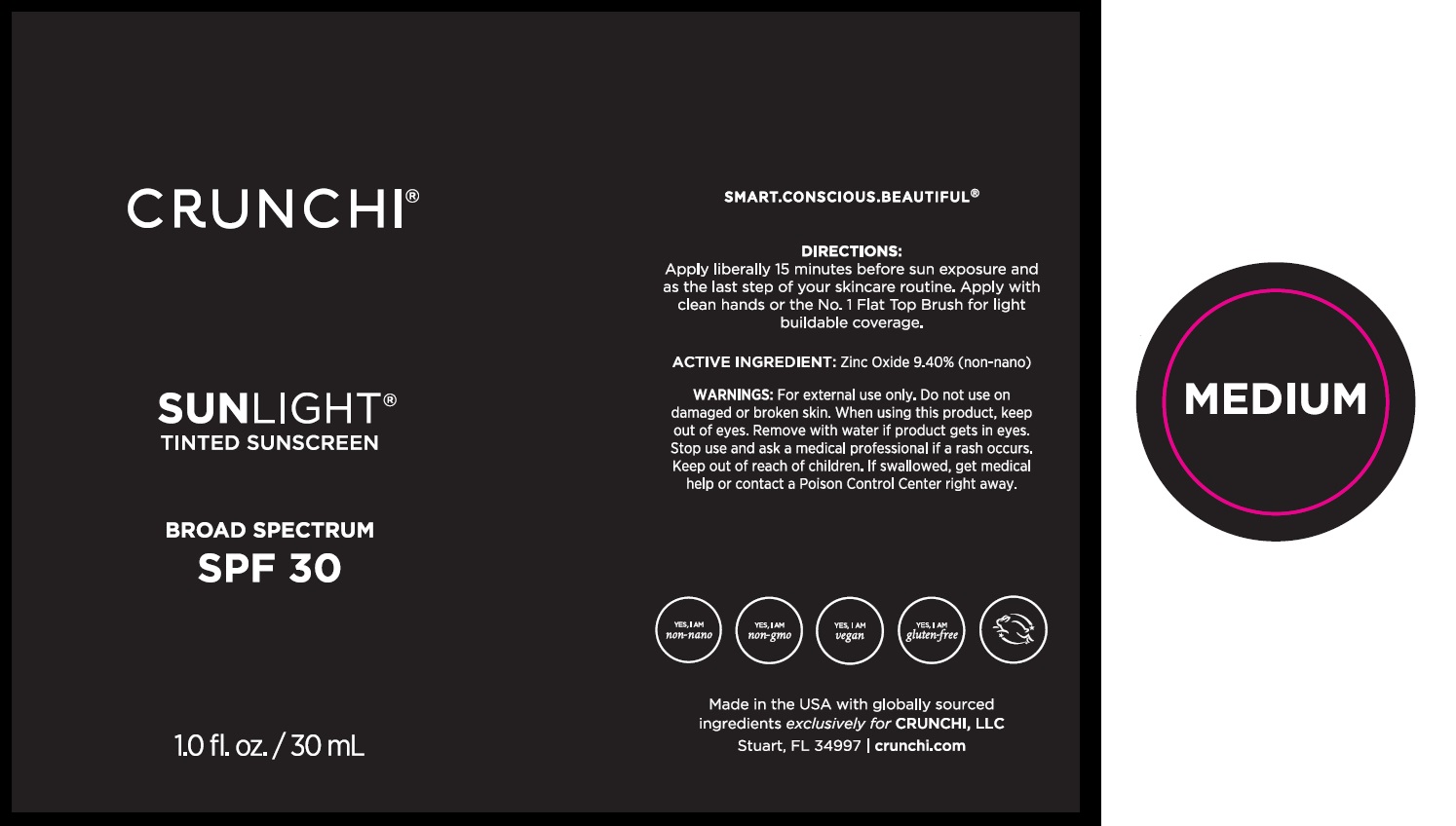 DRUG LABEL: Crunchi Sunlight Tinted Sunscreen SPF 30 Medium
NDC: 72444-0204 | Form: LIQUID
Manufacturer: Crunchi, LLC.
Category: otc | Type: HUMAN OTC DRUG LABEL
Date: 20251215

ACTIVE INGREDIENTS: ZINC OXIDE 940 mg/1 mL
INACTIVE INGREDIENTS: WATER; COCONUT ALKANES; POLYGLYCERYL-6 POLYRICINOLEATE; GLYCERIN; DIMETHICONE, UNSPECIFIED; CETYL ETHYLHEXANOATE; POLYGLYCERYL-2 ISOSTEARATE; DISTEARDIMONIUM HECTORITE; COCO-CAPRYLATE/CAPRATE; PROPANEDIOL; NIACINAMIDE; 1,2-HEXANEDIOL; JOJOBA OIL; SODIUM CHLORIDE; TRIBEHENIN; MAGNESIUM SULFATE, UNSPECIFIED FORM; 3-O-ETHYL ASCORBIC ACID; SQUALANE; GLYCERYL STEARATE SE; TRIETHOXYCAPRYLYLSILANE; XANTHAN GUM; ETHYL FERULATE; SUNFLOWER OIL; HYALURONATE SODIUM; CAPRYLHYDROXAMIC ACID; TOCOPHEROL; .BETA.-SITOSTEROL; SQUALENE

Crunchi Sunlight Tinted Sunscreen SPF 30, Medium

Active Ingredient

Zinc Oxide 9.40%

Purpose

Sunscreen

Uses

- Helps prevent sunburn.
- If used as directed with other sun protection measures (see Directions), decreases the risk of skin cancer and early skin aging caused by the sun.

Warnings

- For external use only.

• Do not use

on damaged or broken skin.

• When using this product

keep out of eyes. Rinse with water to remove.

• Stop use and ask a medical professional if

a rash occurs.

• Keep out of reach of children.

- If swallowed,get medical help or contact a Poison Control Center right away.

Directions

- Apply liberally 15 minutes before sun exposure.
- Re-apply after swimming or sweating.
- Re-apply immediately after towel drying.
- Re-apply at least every 2 hours.
- Children under 6 months of age: Ask a medical professional.

Sun Protection Measures

Spending time in the sun increases your risk of skin cancer and early skin aging. To decrease the risk, regularly use a sunscreen with a Broad Spectrum SPF value of 15 or higher and other sun protection measures including:

- Limit time in the sun, especially from 10 a.m. to 2 p.m.
- Wear long-sleeved shirts, pants, hats, and sunglasses.

Other Information

- Protect the product in this container from excessive heat and direct sun.

Inactive Ingredients

Water/Aqua/Eau, Coconut Alkanes, Polyglyceryl-6 Polyricinoleate, Glycerin, Dimethicone, Cetyl Ethylhexanoate, Polyglyceryl-2 Isostearate, Disteardimonium Hectorite, Coco-Caprylate/Caprate, Propanediol, Niacinamide, 1,2-Hexanediol, Simmondsia Chinensis (Jojoba) Seed Oil, Sodium Chloride, Tribehenin, Magnesium Sulfate, 3-O-Ethyl Ascorbic Acid, Squalane, Glyceryl Stearate SE, Triethoxycaprylylsilane, Xanthan Gum, Ethyl Ferulate, Hydrogenated Lecithin, Helianthus Annuus Seed Oil, Sodium Hyaluronate, Caprylhydroxamic Acid, Tocopherol, Beta Sitosterol**, Squalene**, May Contain (+/-): Titanium Dioxide (CI 77891), Mica (CI 77019), Iron Oxide (CI 77492), Iron Oxide (CI 77491), Iron Oxide (CI 77499)

**Incidental Ingredients

Questions or comments?

www.crunchi.com (888) 831-3133